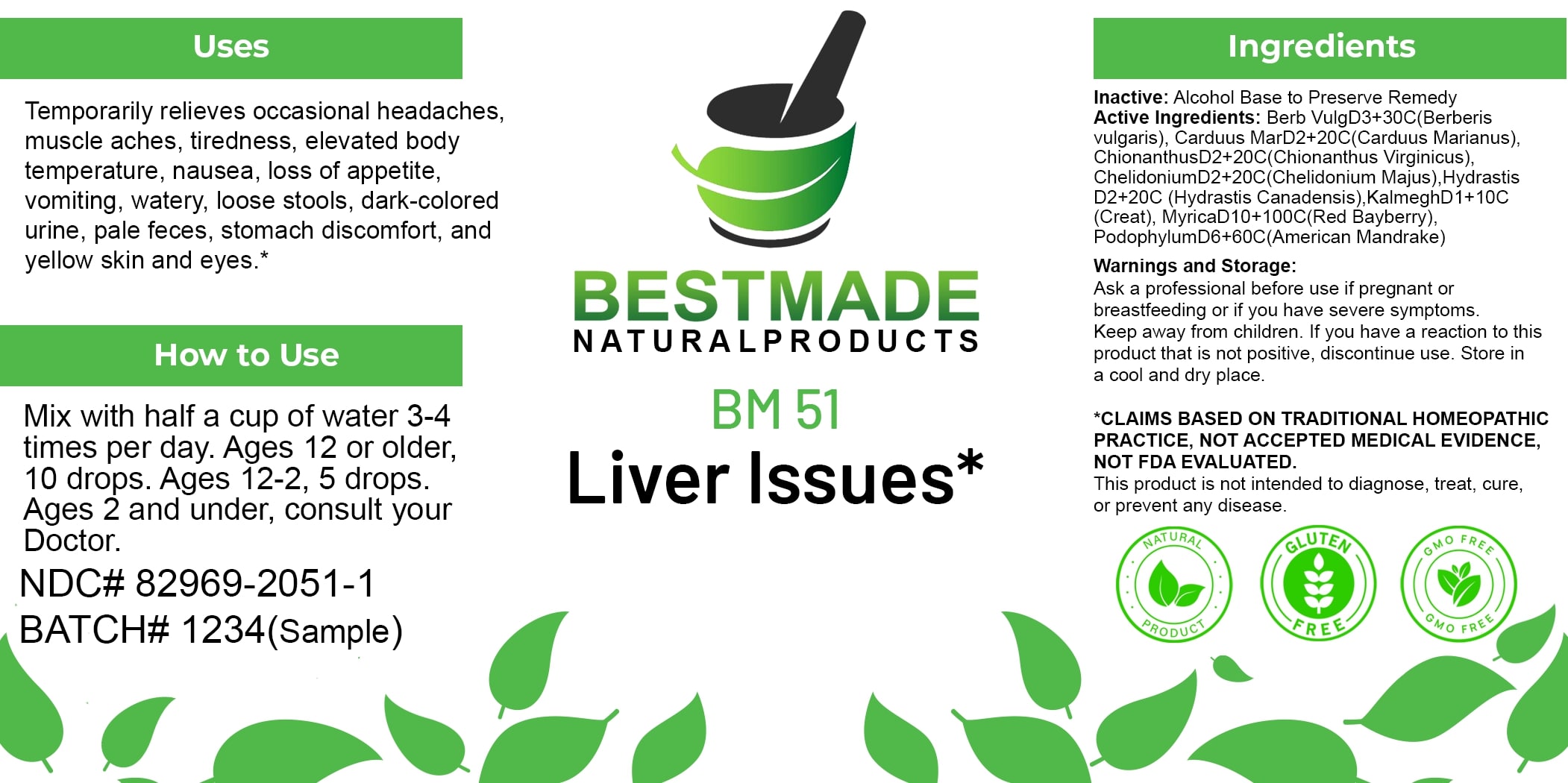 DRUG LABEL: Bestmade Natural Products BM51
NDC: 82969-2051 | Form: LIQUID
Manufacturer: Bestmade Natural Products
Category: homeopathic | Type: HUMAN OTC DRUG LABEL
Date: 20250123

ACTIVE INGREDIENTS: CHELIDONIUM MAJUS 30 [hp_C]/30 [hp_C]; MILK THISTLE 30 [hp_C]/30 [hp_C]; PODOPHYLLUM 30 [hp_C]/30 [hp_C]; MORELLA CERIFERA ROOT BARK 30 [hp_C]/30 [hp_C]; GOLDENSEAL 30 [hp_C]/30 [hp_C]; ANDROGRAPHIS PANICULATA TOP 30 [hp_C]/30 [hp_C]; BERBERIS VULGARIS ROOT BARK 30 [hp_C]/30 [hp_C]; CHIONANTHUS VIRGINICUS ROOT BARK 30 [hp_C]/30 [hp_C]
INACTIVE INGREDIENTS: ALCOHOL 30 [hp_C]/30 [hp_C]

BM51

DOSAGE AND ADMINISTRATION

How to Use

Mix with half a cup of water 3-4 times per day. Ages 12 or older, 10 drops. Ages 12-2, 5 drops. Ages 2 and under, consult your Doctor.

ACTIVE INGREDIENT

Active Ingredients: Berb Vulg D3+30C (Berberis vulgaris), Carduus Mar D2+20C (Carduus Marianus), Chionanthus D2+20C (Chionanthus Virginicus), Chelidonium D2+20C (Chelidonium Majus), Hydrastis D2+20C (Hydrastis Canadensis), Kalmegh D1+10C (Creat), Myrica D10+100C (Red Bayberry), Podophyllum D6+60C (American Mandrake)

INACTIVE INGREDIENT

Ingredients

Inactive: Alcohol Base to Preserve Remedy

Uses

Temporarily relieves occasional headaches, muscle aches, tiredness, elevated body temperature, nausea, loss of appetite, vomiting, watery, loose stools, dark-colored urine, pale feces, stomach discomfort, and yellow skin and eyes.*

*CLAIMS BASED ON TRADITIONAL HOMEOPATHIC PRACTICE, NOT ACCEPTED MEDICAL EVIDENCE, NOT FDA EVALUATED.

This product is not intended to diagnose, treat, cure, or prevent any disease.

Uses

Temporarily relieves occasional headaches, muscle aches, tiredness, elevated body temperature, nausea, loss of appetite, vomiting, watery, loose stools, dark-colored urine, pale feces, stomach discomfort, and yellow skin and eyes.*

*CLAIMS BASED ON TRADITIONAL HOMEOPATHIC PRACTICE, NOT ACCEPTED MEDICAL EVIDENCE, NOT FDA EVALUATED.

This product is not intended to diagnose, treat, cure, or prevent any disease.

KEEP OUT OF REACH OF CHILDREN

Warnings and Storage:

Ask a professional before use if pregnant or breastfeeding or if you have severe symptoms. Keep away from children. If you have a reaction to this product that is not positive, discontinue use. Store in a cool and dry place.

Warnings and Storage:

Ask a professional before use if pregnant or breastfeeding or if you have severe symptoms. Keep away from children. If you have a reaction to this product that is not positive, discontinue use. Store in a cool and dry place.

*CLAIMS BASED ON TRADITIONAL HOMEOPATHIC PRACTICE, NOT ACCEPTED MEDICAL EVIDENCE, NOT FDA EVALUATED.

This product is not intended to diagnose, treat, cure, or prevent any disease.

Entire package label